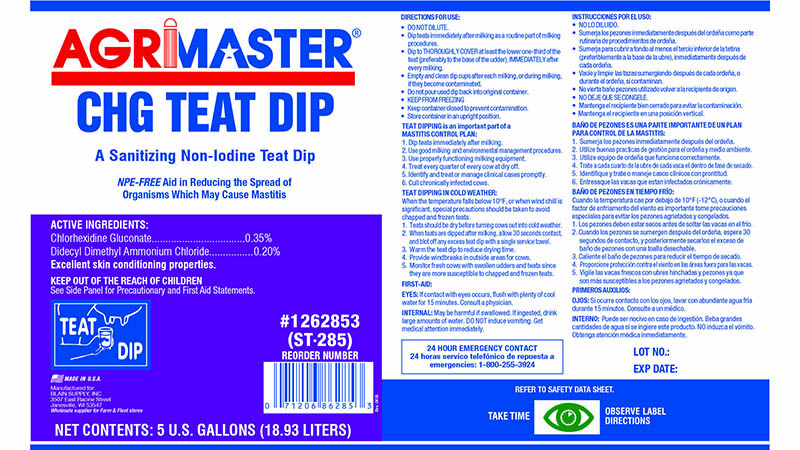 DRUG LABEL: Agrimaster Brand CHG Teat Dip
NDC: 60282-3080 | Form: LIQUID
Manufacturer: Stearns Packaging Corporation
Category: animal | Type: OTC ANIMAL DRUG LABEL
Date: 20251201

ACTIVE INGREDIENTS: CHLORHEXIDINE GLUCONATE 3.5 g/1 L; DIDECYLDIMONIUM CHLORIDE 2 g/1 L
INACTIVE INGREDIENTS: FD&C BLUE NO. 1

CHG Teat Dip

GENERAL PRECAUTIONS

TEAT DIPPING is an important part of a
MASTITIS CONTROL PLAN:

1. Dip teats immediately after milking.
2. Use good milking and environmental management procedures.
3. Use properly functioning milking equipment.
4. Treat every quarter of every cow at dry off.
5. Identify and treat or manage clinical cases promptly.
6. Cull chronically infected cows.

TEAT DIPPING IN COLD WEATHER:
When the temperature falls below 10 degrees F, or when wind chill is
significant,special precautions should be taken to avoid
chapped and frozen teats.
1. Teats should be dry before turning cows out into cold weather.
2. When teats are dipped after milking, allow 30 seconds contact,
and blot off any excess teat dip with a single service towel.
3. Warm the teat dip to reduce drying time.
4. Provide windbreaks in outside areas for cows.
5. Monitor fresh cows with swollen udders and teats since
they are more susceptible to chapped and frozen teats.

REFER TO SAFETY DATA SHEET

TAKE TIME OBSERVE LABEL
DIRECTIONS

DOSAGE AND ADMINISTRATION

DIRECTIONS FOR USE:
• DO NOT DILUTE.
• Dip teats immediately after milking as a routine part of milking
procedures.
• Dip to THOROUGHLY COVER at least the lower one-third of the
teat (preferably to the base of the udder), IMMEDIATELY after
every milking.

STORAGE AND HANDLING

• Empty and clean dip cups after each milking, or during milking,
if they become contaminated.
• Do not pour used dip back into original container.
• KEEP FROM FREEZING
• Keep container closed to prevent contamination.
• Store container in an upright position.

USER SAFETY WARNINGS

FIRST-AID:
EYES: If contact with eyes occurs, flush with plenty of cool
water for 15 minutes. Consult a physician.
INTERNAL: May be harmful if swallowed. If ingested, drink
large amounts of water or milk. DO NOT induce vomiting. Get
medical attention immediately.

24 HOUR EMERGENCY CONTACT

1-800-255-3924

PACKAGE LABEL

AGRIMASTER
CHG TEAT DIP

A Sanitizing Non-Iodine Teat Dip

NPE-FREE Aid in Reducing the Spread of
Organisms Which May Cause Mastitis.

ACTIVE INGREDIENTS:
Chlorhexidine Gluconate..........................................0.35%
Didecyl Dimethyl Ammonium Chloride........................0.20%
Excellent skin conditioning properties.

KEEP OUT OF THE REACH OF CHILDREN
See Side Panel for Precautionary and First Aid Statements.

TEAT DIP

MADE IN USA

Manufactured for:
BLAIN SUPPLY, INC.
3507 East Racine Street
Janesville, WI 53547
Wholesale supplier for Farm & Fleet stores

NET CONTENTS: 5 U.S. GALLONS (18.93 LITER)